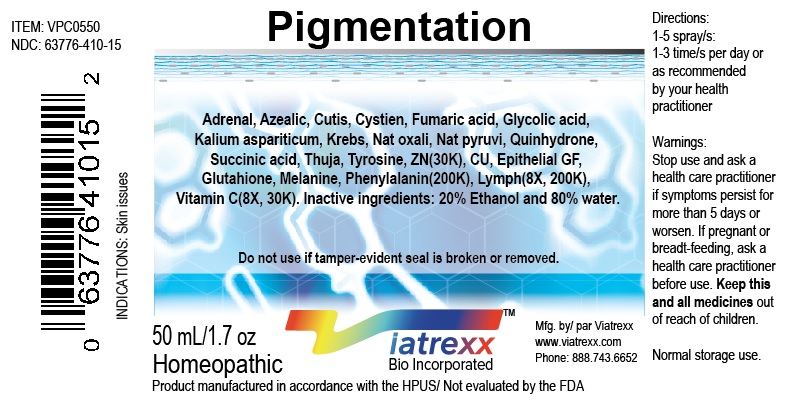 DRUG LABEL: Viatrexx-Pigmentation
NDC: 63776-410 | Form: SPRAY
Manufacturer: VIATREXX BIO INCORPORATED
Category: homeopathic | Type: HUMAN OTC DRUG LABEL
Date: 20190319

ACTIVE INGREDIENTS: Sus Scrofa Adrenal Gland 30 [kp_C]/1 mL; Bos Taurus Adrenal Gland 30 [kp_C]/1 mL; Azelaic Acid 30 [kp_C]/1 mL; Bos Taurus Skin 30 [kp_C]/1 mL; Copper 200 [kp_C]/1 mL; Cysteine 30 [kp_C]/1 mL; Fumaric Acid 30 [kp_C]/1 mL; Glutathione 200 [kp_C]/1 mL; Glycolic Acid 30 [kp_C]/1 mL; Potassium Aspartate 30 [kp_C]/1 mL; Nepidermin 200 [kp_C]/1 mL; Sus Scrofa Lymph Vessel 200 [kp_C]/1 mL; Bos Taurus Lymph Vessel 200 [kp_C]/1 mL; Sodium Diethyl Oxalacetate 30 [kp_C]/1 mL; Sodium Pyruvate 30 [kp_C]/1 mL; Phenylalanine 200 [kp_C]/1 mL; Quinhydrone 30 [kp_C]/1 mL; Succinic Acid 30 [kp_C]/1 mL; Thuja Occidentalis Leafy Twig 30 [kp_C]/1 mL; Tyrosine 30 [kp_C]/1 mL; Ascorbic Acid 30 [kp_C]/1 mL; Zinc 30 [kp_C]/1 mL; Melanin Synthetic (Tyrosine, Peroxide) 200 [kp_C]/1 mL; Sus Scrofa Skin 30 [kp_C]/1 mL
INACTIVE INGREDIENTS: Alcohol; Water

Pigmentation

Active Ingredients

Adrenal (30K), Azelaic (30K), Copper (200K), Cutis (30K), Cysteine (30K), Epithelial GF (200K) Fumaric acid (30K) Glutathione (200K), Glycolic acid (30K) Kalium aspariticum (30K) Lymph node (8X, 200K), Melanine (200K), Natrum Oxalicum (30K), Natrum Pyruvicum (30K), Phenylalanine (200K), Quinhydrone (30K), Succinic acid (30K), Thuja (30K), Tyrosine (30K), Vitamin C (8X, 30K), Zinc (30K).

Purpose

Adrenal
Azelaic
Copper
Cutis
Cystein
Epithelial GF
Fumaric acid
Glutathione
Glycolic acid
Kalium aspariticum
Lymph node
Melanine
Natrum Oxalicum
Natrum Pyruvicum
Phenylalanine
Quinhydrone
Succinic acid
Thuja
Tyrosine
Vitamin C
Zinc

Adrenal support
Adaptogen
Nutritional support
Regeneration
Drainage
Regeneration
Cell respiration
Anti-oxidant
Cell respiration
Cell respiration
Immune support
Neurological support
Cell respiration
Cell respiration
Amino Acid Support
Cell respiration
Cell respiration
Drainage
Amino Acid Support
Nutritional support
Neurological support

Description

Viatrexx-Pigmentation is a homeopathic product composed of physiological (low dose and low low dose) natural micro nutrients. These nano particles are designed to nourish the system.

Uses

Skin Issues

Warnings

Stop use and ask a health care practitioner if symptoms persist for more than 5 days or worsen. If pregnant or breastfeeding, ask a health care practitioner before use.

Dosage

1-5 spray(s); 1-3 time(s) per day or as recommended by your health care practitioner.

Inactive Ingredients

Alcohol 20% and Water 80%

Product availability

Product may be acquired in 0.5, 30 ,50, 100, 250, 500, 1,000 mL bottles.

Other Information

Normal storage use.
Do not use if tamper-evident seal is broken or removed.

To report SUSPECTED ADVERSE REACTIONS, contact the FDA at 1-800-FDA-1088 or www.fda.gov/medwatch

Distributed by
Viatrexx Bio Incorporated
Newark, DE, USA, 19713

Manufactured by
8046255 Canada Inc
Beloeil, Qc, J3G 6S3
Date of last revision March 2019

For Questions and comments
Info@Viatrexx.com
www.Viatrexx.com

PACKAGE LABEL.PRINCIPAL DISPLAY PANEL

NDC: 63776-410-11
Item: VPC0550
Viatrexx Bio Incorporated
Viatrexx-Pigmentation
0.5 mL ampule
For Oral and Topical Use
Expiry date: Lot #:
Manufactured for:
Viatrexx Bio Incorporated Newark, DE, USA, 19713
www.Viatrexx.com
Ingredients, homeopathic
See insert or www.viatrexx.com
Inactives: Alcohol 20%, Water 80%

NDC: 63776-410-14
Item: VPC0550
Viatrexx Bio Incorporated
Viatrexx-Pigmentation
30 mL spray bottle
For Oral and Topical Use
Expiry date: Lot #:
Manufactured for:
Viatrexx Bio Incorporated Newark, DE, USA, 19713
www.Viatrexx.com
Ingredients, homeopathic
See insert or www.viatrexx.com
Inactives: Alcohol 20%, Water 80%

NDC: 63776-410-15
Item: VPC0550
Viatrexx Bio Incorporated
Viatrexx-Pigmentation
50 mL spray bottle
For Oral and Topical Use
Expiry date: Lot #:
Manufactured for:
Viatrexx Bio Incorporated Newark, DE, USA, 19713
www.Viatrexx.com
Ingredients, homeopathic
See insert or www.viatrexx.com
Inactives: Alcohol 20%, Water 80%

NDC: 63776-410-16
Item: VPC0550
Viatrexx Bio Incorporated
Viatrexx-Pigmentation
100 mL bottle
For Oral and Topical Use
Expiry date: Lot #:
Manufactured for:
Viatrexx Bio Incorporated Newark, DE, USA, 19713
www.Viatrexx.com
Ingredients, homeopathic
See insert or www.viatrexx.com
Inactives: Alcohol 20%, Water 80%

NDC: 63776-410-17
Item: VPC0550
Viatrexx Bio Incorporated
Viatrexx-Pigmentation
250 mL bottle
For Oral and Topical Use
Expiry date: Lot #:
Manufactured for:
Viatrexx Bio Incorporated Newark, DE, USA, 19713
www.Viatrexx.com
Ingredients, homeopathic
See insert or www.viatrexx.com
Inactives: Alcohol 20%, Water 80%